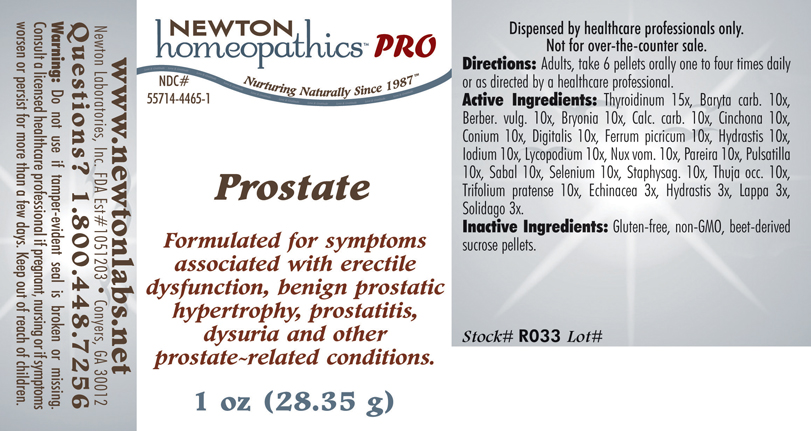 DRUG LABEL: Prostate 
NDC: 55714-4465 | Form: PELLET
Manufacturer: Newton Laboratories, Inc.
Category: homeopathic | Type: HUMAN PRESCRIPTION DRUG LABEL
Date: 20110601

ACTIVE INGREDIENTS: Thyroid, Unspecified 15 [hp_X]/1 g; Barium Carbonate 10 [hp_X]/1 g; Berberis Vulgaris Root Bark 10 [hp_X]/1 g; Bryonia Alba Root 10 [hp_X]/1 g; Oyster Shell Calcium Carbonate, Crude 10 [hp_X]/1 g; Cinchona Officinalis Bark 10 [hp_X]/1 g; Conium Maculatum Flowering Top 10 [hp_X]/1 g; Digitalis 10 [hp_X]/1 g; Goldenseal 10 [hp_X]/1 g; Iodine 10 [hp_X]/1 g; Lycopodium Clavatum Spore 10 [hp_X]/1 g; Strychnos Nux-vomica Seed 10 [hp_X]/1 g; Chondrodendron Tomentosum Root 10 [hp_X]/1 g; Pulsatilla Vulgaris 10 [hp_X]/1 g; Saw Palmetto 10 [hp_X]/1 g; Selenium 10 [hp_X]/1 g; Delphinium Staphisagria Seed 10 [hp_X]/1 g; Thuja Occidentalis Leafy Twig 10 [hp_X]/1 g; Trifolium Pratense Flower 10 [hp_X]/1 g; Echinacea, Unspecified 3 [hp_X]/1 g; Arctium Lappa Root 3 [hp_X]/1 g; Solidago Virgaurea Flowering Top 3 [hp_X]/1 g; Ferric Picrate 10 [hp_X]/1 g
INACTIVE INGREDIENTS: Sucrose

Prostate

INDICATIONS & USAGE SECTION

Prostate Formulated for symptoms associated with erectile dysfunction, benign prostatic hypertrophy, prostatitis, dysuria and other prostate related conditions.

DOSAGE & ADMINISTRATION SECTION

Directions: Adults, take 6 pellets orally one to four times daily or as directed by a healthcare professional.

ACTIVE INGREDIENT SECTION

Thyroidinum 15x, Baryta carb. 10x , Berber. vulg. 10x, Bryonia 10x, Calc. carb. 10x, Cinchona 10x , Conium 10x, Digitalis 10x, Ferrum picricum 10x, Hydrastis 10x, Iodium 10x, Lycopodium 10x, Nux vom. 10x, Pareira 10x, Pulsatilla 10x, Sabal 10x, Selenium 10x, Staphysag. 10x, Thuja occ. 10x, Trifolium pratense 10x, Echinacea 3x, Hydrastis 3x, Lappa 3x, Solidago 3x.

PURPOSE SECTION

Formulated for symptoms associated with erectile dysfunction, benign prostatic hypertrophy, prostatitis, dysuria and other prostate related conditions.

INACTIVE INGREDIENT SECTION

Gluten-free,non-GMO, beet-derived sucrose pellets.

QUESTIONS? SECTION

www.newtonlabs.net Newton Laboratories, Inc. FDA Est # 1051203 - Conyers, GA30012
Questions? 1.800.448.7256

WARNINGS SECTION

Warning: Do not use if tamper - evident seal is broken or missing. Consult a licensed healthcare professional if pregnant, nursing or if symptoms worsen or persist for more than a few days. Keep out of reach of children.

PREGNANCY OR BREAST FEEDING SECTION

Consult a licensed healthcare professional if pregnant, nursing or if symptoms worsen or persist for more than a few days.

KEEP OUT OF REACH OF CHILDREN SECTION

Keep out of reach of children